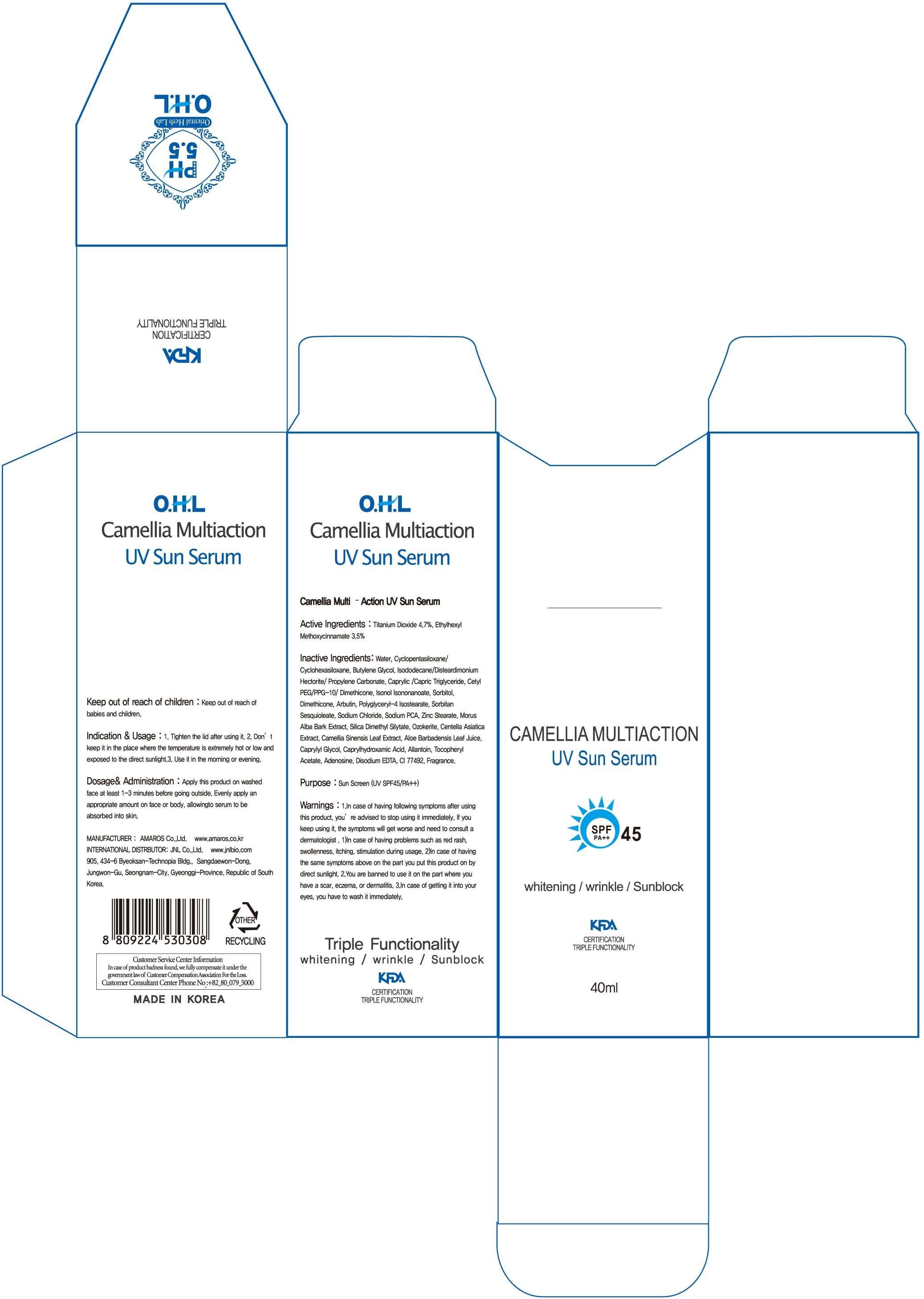 DRUG LABEL: Camellia Multiaction UV Sun Serum
NDC: 60899-030 | Form: CREAM
Manufacturer: AMAROS CO., LTD.
Category: otc | Type: HUMAN OTC DRUG LABEL
Date: 20190411

ACTIVE INGREDIENTS: Titanium Dioxide 1.88 mg/40 mL; OCTINOXATE 1.4 mg/40 mL
INACTIVE INGREDIENTS: Water; Butylene Glycol

ACTIVE INGREDIENT

Active Ingredients: Titanium Dioxide 4.7%, Ethylhexyl Methoxycinnamate 3.5%

INACTIVE INGREDIENT

Inactive Ingredients: Water, Cyclopentasiloxane/ Cyclohexasiloxane, Butylene Glycol, Isododecane/Disteardimonium Hectorite/ Propylene Carbonate, Caprylic /Capric Triglyceride, Cetyl PEG/PPG-10/ Dimethicone, Isonol Isononanoate, Sorbitol, Dimethicone, Arbutin, Polyglyceryl-4 Isostearate, Sorbitan Sesquioleate, Sodium Chloride, Sodium PCA, Zinc Stearate, Morus Alba Bark Extract, Silica Dimethyl Silytate, Ozokerite, Centella Asiatica Extract, Camellia Sinensis Leaf Extract, Aloe Barbadensis Leaf Juice, Caprylyl Glycol, Caprylhydroxamic Acid, Allantoin, Tocopheryl Acetate, Adenosine, Disodium EDTA, CI 77492, Fragrance.

PURPOSE

Purpose: Sun Screen (UV SPF45/PA++)

WARNINGS

Warnings: 1. In case of having following symptoms after using this product, you're advised to stop using it immediately. If you keep using it, the symptoms will get worse and need to consult a dermatologist. 1) In case of having problems such as red rash, swollenness, itching, stimulation during usage. 2) In case of having the same symptoms above on the part you put this product on by direct sunlight. 2. You are banned to use it on the part where you have a scar, eczema, or dermatitis. 3. In case of getting it into your eyes, you have to wash it immediately.

Keep out of reach of children: Keep out of reach of babies and children.

INDICATIONS AND USAGE

Indication and Usage: 1. Tighten the lid after using it. 2. Don't keep it in the place where the temperature is extremely hot or low and exposed to the direct sunlight. 3. Use it in the morning or evening.

Dosage and Administration: Apply this product on washed face at least 1-3 minutes before going outside. Evenly apply an appropriate amount on face or body, allowing to serum to be absorbed into skin.